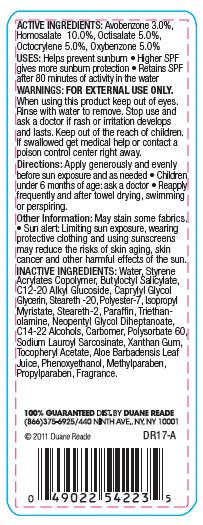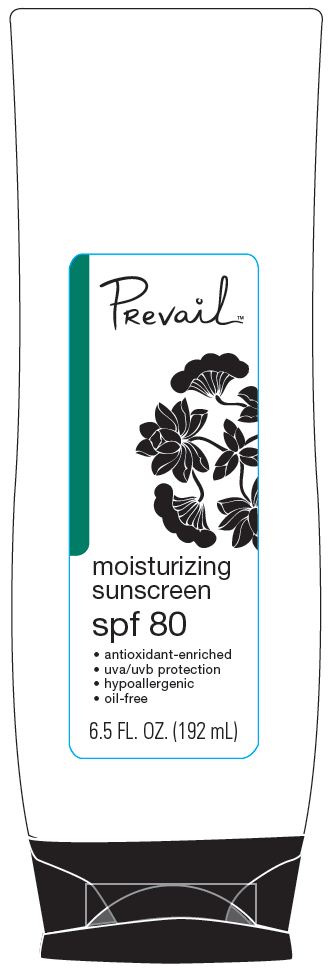 DRUG LABEL: Duane Reade Prevail Moisturizing Sunscreen
NDC: 67732-413 | Form: LOTION
Manufacturer: DUANE READE INC.
Category: otc | Type: HUMAN OTC DRUG LABEL
Date: 20121114

ACTIVE INGREDIENTS: AVOBENZONE 3 g/100 g; OCTOCRYLENE 5 g/100 g; OXYBENZONE 5 g/100 g; HOMOSALATE 10 g/100 g; OCTISALATE 5 g/100 g
INACTIVE INGREDIENTS: WATER; BUTYLOCTYL SALICYLATE ; C12-20 ALKYL GLUCOSIDE; CAPRYLYL GLYCOL; GLYCERIN; STEARETH-20; POLYESTER-7; ISOPROPYL MYRISTATE; STEARETH-2; PARAFFIN; TROLAMINE; NEOPENTYL GLYCOL DIHEPTANOATE; C14-22 ALCOHOLS; POLYSORBATE 60; SODIUM LAUROYL SARCOSINATE; ALOE VERA LEAF; XANTHAN GUM; VITAMIN A PALMITATE; PHENOXYETHANOL; METHYLPARABEN; PROPYLPARABEN

ACTIVE INGREDIENTS:

Avobenzone 3.0 %

Homosalate 10.0%

Octisalate 5.0%

Octocrylene 5.0 %

Oxybenzone 5.0%

Purpose

Sunscreen

USES:

- Helps prevent sunburn
- Higher SPF gives more sunburn protection
- Retains SPF after 80 minutes of activity in the water

WARNINGS:

FOR EXTERNAL USE ONLY.

When using this product

keep out of eyes. Rinse with water to remove.

Stop use and ask a doctor if

rash or irritation develops and lasts

KEEP OUT OF REACH OF CHILDREN

keep out of the reach of children. If swallowed get medical help or contact a poison control center right away.

Directions:

Apply generously and evenly before sun exposure and as needed

- Children under 6 months of age:ask a doctor
- Reapply frequently and after towel drying, swimming or perspiring.

Other Information:

May stain some fabrics.

- Sun Alert: Limiting sun exposure, wearing, protective clothing, and using sunscreens may reduce the risks of skin aging, skin cancer, and other harmful effects of the sun.

INACTIVE INGREDIENTS:

Water, Styrene Acrylates Copolymer, Butyloctyl Salicylate, C12-20 Alkyl Glucoside, Caprylyl Glycol, Glycerin, Steareth-20, Polyester-7, Isopropyl Myristate, Steareth-2, Paraffin, Triethanolamine, Neopentyl Glycol Diheptanoate, C14-22 Alcohols, Carbomer, Polysorbate 60, Sodium Lauroyl Sarcosinate, Xanthan Gum, Tocopheryl Acetate, Aloe Barbadensis Leaf Juice, Phenoxyethanol, Methylparaben, Propylparaben, Fragrance.

Principal Display Panel

PRevail

moisturizing sunscreen

spf 80

- antioxidant-enriched
- uva/uvb protection
- hypoallergic
- oil-free

6.5 FL. OZ. (192 mL)